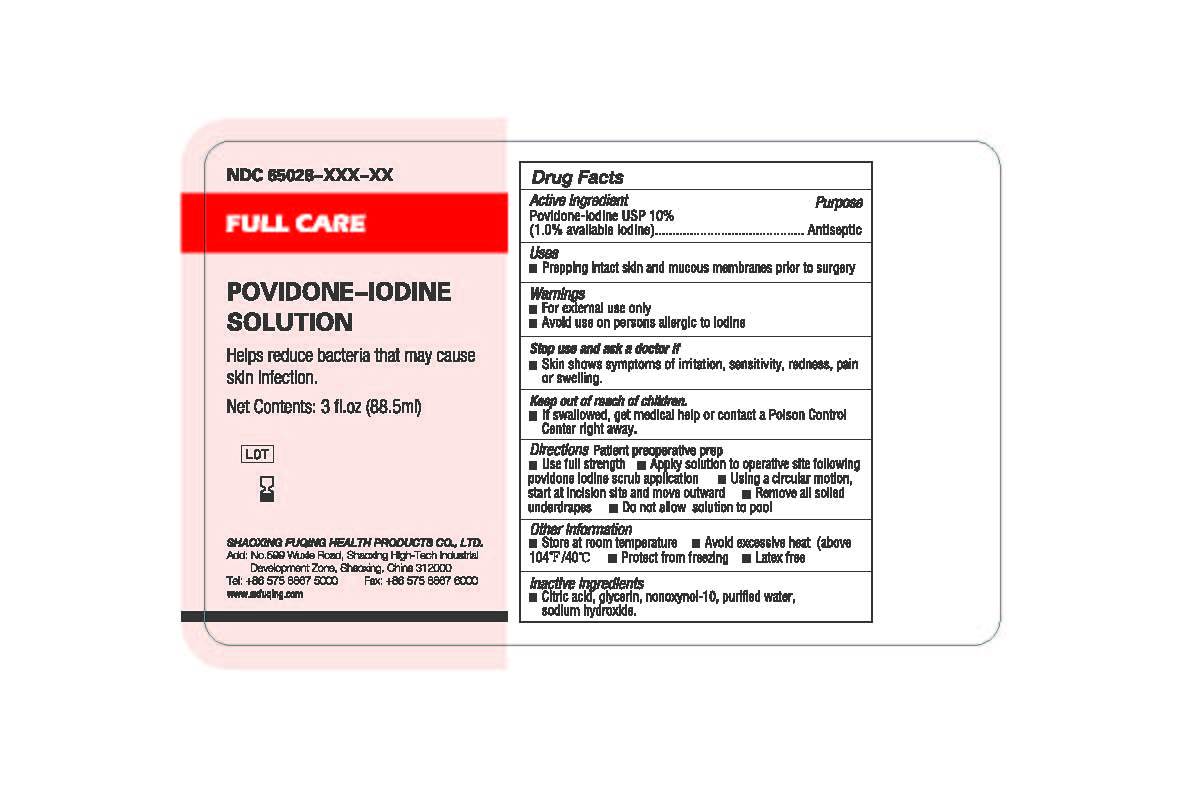 DRUG LABEL: Full Care  Povidone Iodine Solution
NDC: 65028-006 | Form: SOLUTION
Manufacturer: Shaoxing Fuqing Health Products Co., Ltd.
Category: otc | Type: HUMAN OTC DRUG LABEL
Date: 20140929

ACTIVE INGREDIENTS: POVIDONE-IODINE 1 g/100 mL
INACTIVE INGREDIENTS: WATER; CITRIC ACID MONOHYDRATE; SODIUM HYDROXIDE; GLYCERIN; NONOXYNOL-10

Active Ingredient: Povidone-Iodine USP 10% (1.0% Available Iodine)

Purpose: Antiseptic

INDICATIONS AND USAGE

Use: Prepping Intact Skin and Mucous Membranes Prior to Surgery

Warnings:

For external use only

Avoid use on persons allergic to iodine

Keep out of reach of children. If swallowed, get medical help or consult a poison control center right away

Stop use and ask a doctor if

- Skin shows symptoms of irritation, sensitivity, redness, pain, or swelling.

DOSAGE AND ADMINISTRATION

Directions: Patient Preoperative Prep:

Use full strength. Apply solution to preoperative site following povidone iodine scrub application. Use a circular motion,start as incision site and move onward. Remove all soiled underdrapes. Do not allow solution to pool.

Other information

- Store at room temperature.
- Avoid excessive heat (above 104F/40C)
- Protect from freezing)
- Laetx free

Inactive Ingredient

Citric Acid, Glycerin, Nonoxyol-10, Sodium Hydroxide, Water